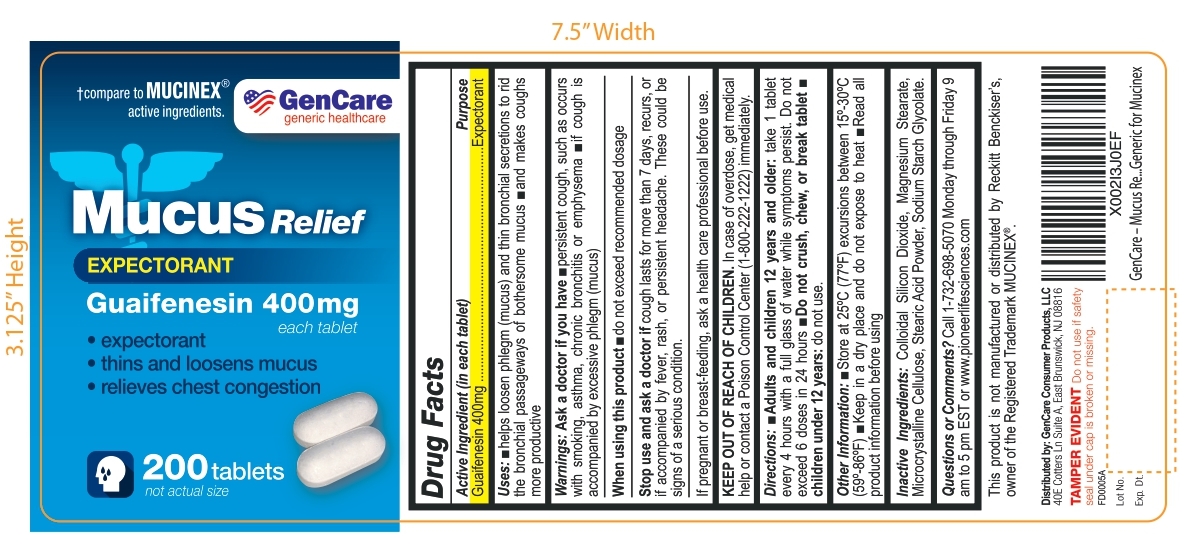 DRUG LABEL: MUCUS RELIEF
NDC: 72090-009 | Form: TABLET
Manufacturer: Pioneer Life Sciences, LLC
Category: otc | Type: HUMAN OTC DRUG LABEL
Date: 20251226

ACTIVE INGREDIENTS: GUAIFENESIN 400 mg/1 1
INACTIVE INGREDIENTS: SILICON DIOXIDE; MAGNESIUM STEARATE; MICROCRYSTALLINE CELLULOSE; STEARIC ACID; SODIUM STARCH GLYCOLATE TYPE A POTATO

MUCUS RELIEF- Guaifenesin 400 mg tablet

Active ingredient (in each tablet)

Guaifenesin 400 mg

Purpose

Expectorant

Uses

- helps loosen phlegm (mucus) and thin bronchial secretions to rid the bronchial passageways of bothersome mucus
- and makes coughs more productive

Warnings

Ask a doctor before use if you have

- persistent cough such as occurs with smoking, asthma, chronic bronchitis or emphysema
- If cough is accompanied by excessive phlegm (mucus)

When using this product

- do not exceed recommended dosage

Stop use and ask a doctor if

cough lasts for more than 7 days, recurs, or if accompanied by fever, rash, or persistent headache. These could be signs of a serious condition.

PREGNANCY OR BREAST FEEDING

If pregnant or breast-feeding,ask a health care professional before use.

KEEP OUT OF REACH OF CHILDREN. In case of overdose, get medical help or contact a Poison Control Center (1-800-222-1222) immediately.

Directions

- Adults and children 12 years and older:take 1 tablet every 4 hours with a full glass of water while symptoms persist. Do not exceed 6 doses in 24 hours.
- Do not crush, chew, or break tablet
- children under 12 years:do not use

Other information

- Store at 25°C (77°F) excursions between 15°-30°C (59°-86°F)
- Keep in a dry place and do not expose to heat
- Read all product information before using

Inactive ingredients

Colloidal Silicon Dioxide, Magnesium Stearate, Microcrystalline Cellulose, Stearic Acid Powder, Sodium Starch Glycolate

Questions or Comments ?

Call 1-732-698-5070 Monday through Friday 9 am to 5 pm EST or www.pioneerlifesciences.com

This product is not manufcatured or distributed by Reckitt Benckiser's , owner of the Registered Trademark MUCINEX®

Distributed by: GenCare Consumer Products, LLC

40E Cotters Ln Suite A, East Brunswick, NJ 08816